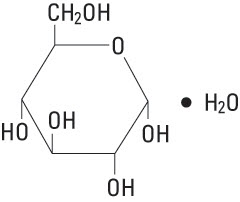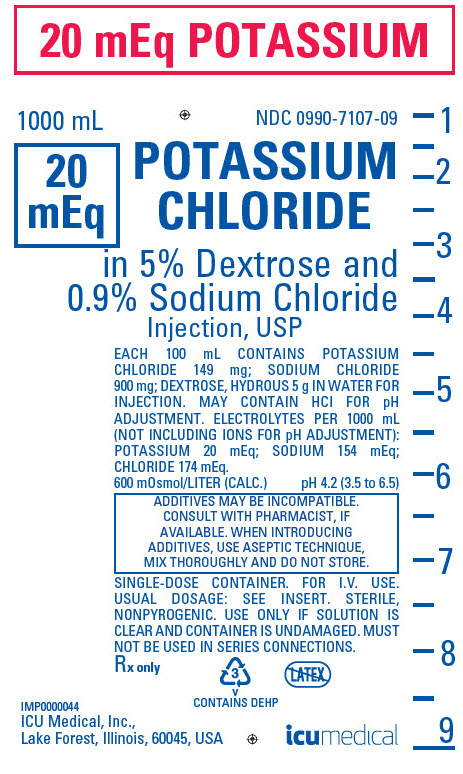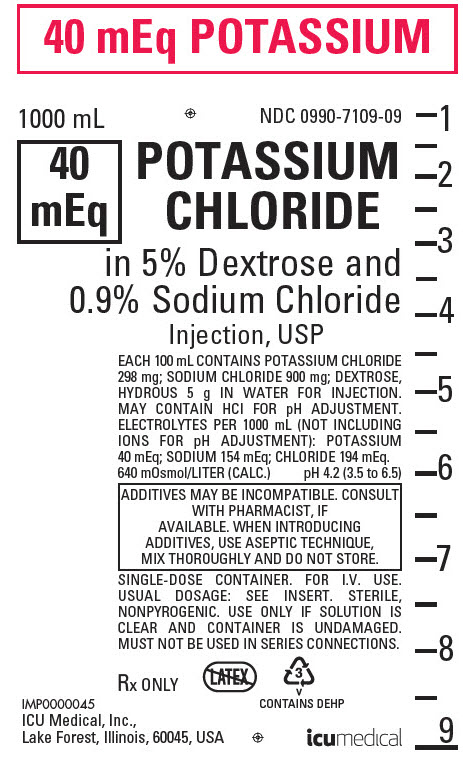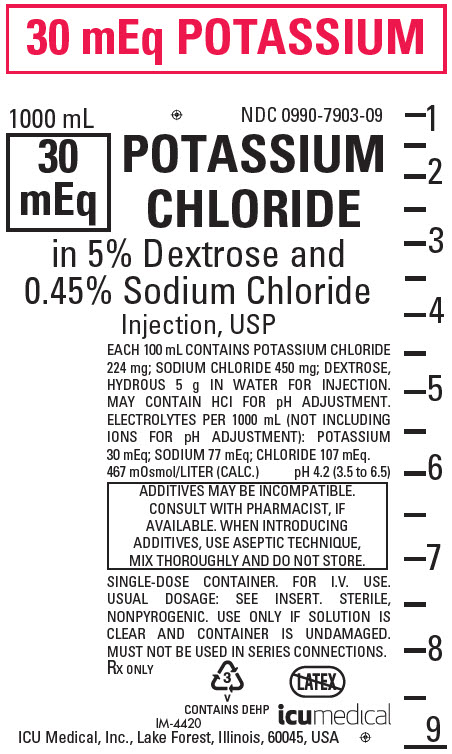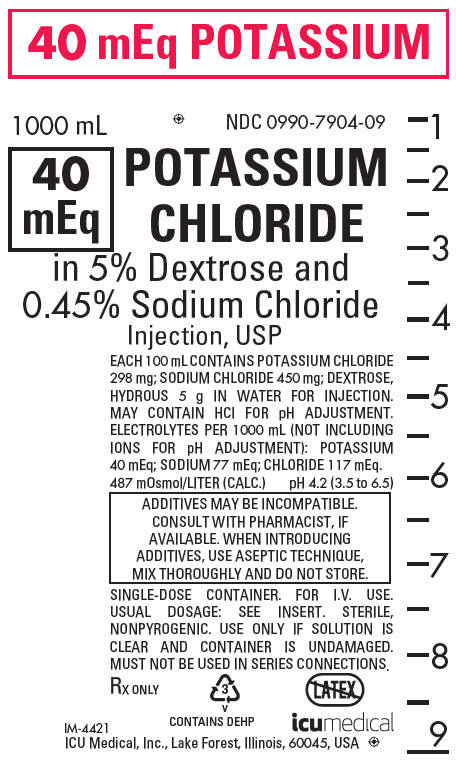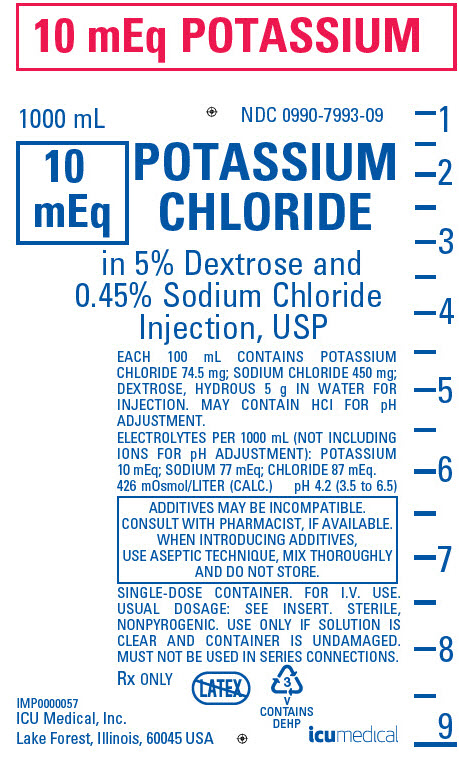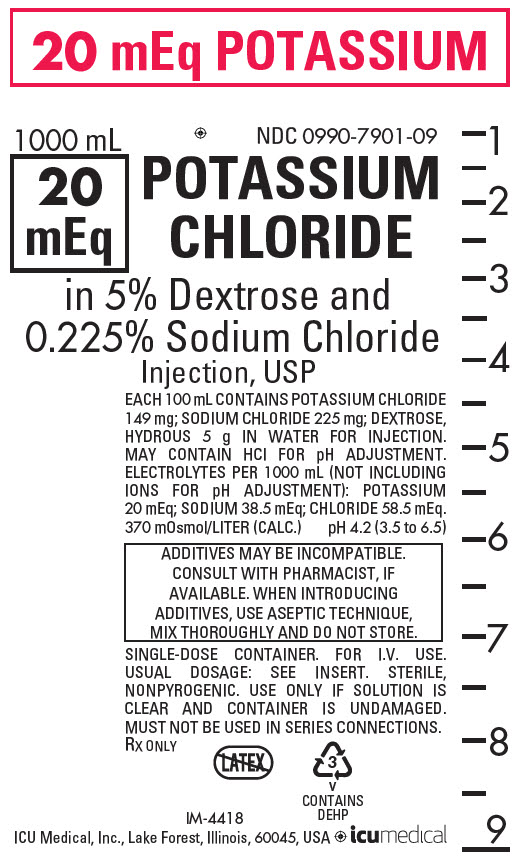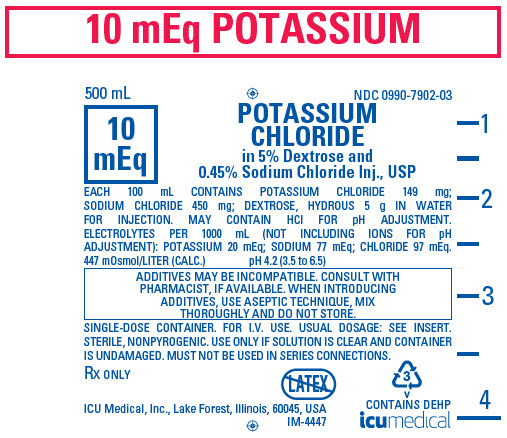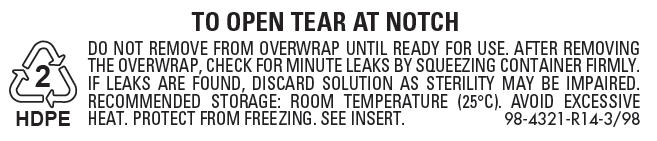 DRUG LABEL: Potassium Chloride in Dextrose and Sodium Chloride
NDC: 0990-7107 | Form: INJECTION, SOLUTION
Manufacturer: ICU Medical Inc.
Category: prescription | Type: HUMAN PRESCRIPTION DRUG LABEL
Date: 20251102

ACTIVE INGREDIENTS: DEXTROSE MONOHYDRATE 50 g/1000 mL; SODIUM CHLORIDE 9 g/1000 mL; POTASSIUM CHLORIDE 1.49 g/1000 mL
INACTIVE INGREDIENTS: WATER; HYDROCHLORIC ACID

INTRAVENOUS SOLUTIONS
WITH POTASSIUM CHLORIDE

Rx only

Potassium Chloride in 5% Dextrose and Sodium Chloride Injection, USP

Flexible Plastic Container

DESCRIPTION

Intravenous solutions with potassium chloride (I.V. solutions with KCl) are sterile and nonpyrogenic solutions in water for injection. They are for administration by intravenous infusion only.

See Tables for summary of content and characteristics of these solutions.

The solutions contain no bacteriostat, antimicrobial agent or added buffer and each is intended only for use as a single-dose injection. When smaller doses are required the unused portion should be discarded.

These solutions are parenteral fluid, nutrient and/or electrolyte replenishers.

Dextrose, USP is chemically designated D-glucose, monohydrate (C6H12O6 • H2O), a hexose sugar freely soluble in water. It has the following structural formula:

Potassium Chloride, USP is chemically designated KCl, a white granular powder freely soluble in water.

Sodium Chloride, USP is chemically designated NaCl, a white crystalline powder freely soluble in water.

Water for Injection, USP is chemically designated H2O.

The flexible plastic container is fabricated from a specially formulated polyvinylchloride. Water can permeate from inside the container into the overwrap but not in amounts sufficient to affect the solution significantly. Solutions in contact with the plastic container may leach out certain chemical components from the plastic in very small amounts; however, biological testing was supportive of the safety of the plastic container materials. Exposure to temperatures above 25°C/77°F during transport and storage will lead to minor losses in the moisture content. Higher temperatures lead to greater losses. It is unlikely that these minor losses will lead to clinically significant changes within the expiration period.

CLINICAL PHARMACOLOGY

When administered intravenously, these solutions provide a source of water and potassium chloride with carbohydrate (dextrose) and sodium chloride. See HOW SUPPLIED section for specific concentrations of these various solutions.

Solutions containing carbohydrate in the form of dextrose restore blood glucose levels and provide calories. Carbohydrate in the form of dextrose may aid in minimizing liver glycogen depletion and exerts a protein-sparing action. Dextrose injected parenterally undergoes oxidation to carbon dioxide and water.

Intravenous solutions containing potassium chloride are particularly intended to provide needed potassium cation (K^+). Potassium is the chief cation of body cells (160 mEq/liter of intracellular water). It is found in low concentration in plasma and extracellular fluids (3.5 to 5.0 mEq/liter in a healthy adult). Potassium plays an important role in electrolyte balance. Normally about 80 to 90% of the potassium intake is excreted in the urine; the remainder in the stools and to a small extent, in the perspiration. The kidney does not conserve potassium well so that during fasting or in patients on a potassium-free diet, potassium loss from the body continues resulting in potassium depletion. A deficiency of either potassium or chloride will lead to a deficit of the other.

Sodium chloride in water dissociates to provide sodium (Na^+) and chloride (Cl^−) ions. Sodium (Na^+) is the principal cation of the extracellular fluid and plays a large part in the therapy of fluid and electrolyte disturbances. Chloride (Cl^−) has an integral role in buffering action when oxygen and carbon dioxide exchange occurs in the red blood cells. The distribution and excretion of sodium (Na^+) and chloride (Cl^−) are largely under the control of the kidney which maintains a balance between intake and output.

Water is an essential constituent of all body tissues and accounts for approximately 70% of total body weight. Average normal adult daily requirement ranges from two to three liters (1.0 to 1.5 liters each for insensible water loss by perspiration and urine production).

Water balance is maintained by various regulatory mechanisms. Water distribution depends primarily on the concentration of electrolytes in the body compartments and sodium (Na^+) plays a major role in maintaining physiologic equilibrium.

INDICATIONS AND USAGE

These solutions are indicated in patients requiring parenteral administration of potassium chloride with minimal carbohydrate calories and sodium chloride.

CONTRAINDICATIONS

Solutions containing potassium chloride are contraindicated in diseases where high potassium levels may be encountered.

WARNINGS

Solutions which contain potassium ions should be used with great care, if at all, in patients with hyperkalemia, severe renal failure and in conditions in which potassium retention is present.

To avoid potassium intoxication, do not infuse these solutions rapidly. In patients with severe renal insufficiency or adrenal insufficiency, administration of potassium chloride may cause potassium intoxication.

Solutions containing sodium ions should be used with great care, if at all, in patients with congestive heart failure, severe renal insufficiency and in clinical states in which there exists edema with sodium retention.

In patients with diminished renal function, administration of solutions containing sodium or potassium ions may result in sodium or potassium retention.

The intravenous administration of these solutions can cause fluid and/or solute overloading resulting in dilution of serum electrolyte concentrations, overhydration, congested states or pulmonary edema.

The risk of dilutional states is inversely proportional to the electrolyte concentration of administered parenteral solutions. The risk of solute overload causing congested states with peripheral and pulmonary edema is directly proportional to the electrolyte concentrations of such solutions.

PRECAUTIONS

Clinical evaluation and periodic laboratory determinations are necessary to monitor changes in fluid balance, electrolyte concentrations and acid-base balance during prolonged parenteral therapy or whenever the condition of the patient warrants such evaluation.

Solutions containing dextrose should be used with caution in patients with known subclinical or overt diabetes mellitus.

Caution must be exercised in the administration of parenteral fluids, especially those containing sodium ions, to patients receiving corticosteroids or corticotropin.

Potassium replacement therapy should be guided primarily by serial electrocardiograms. Plasma potassium levels are not necessarily indicative of tissue potassium levels.

High plasma concentrations of potassium may cause death through cardiac depression, arrhythmias or arrest.

Potassium-containing solutions should be used with caution in the presence of cardiac disease, particularly in digitalized patients or in the presence of renal disease.

Care should be exercised to insure that the needle (or catheter) is well within the lumen of the vein and that extravasation does not occur.

Do not administer unless solution is clear and container is undamaged. Discard unused portion.

Carcinogenesis, Mutagenesis, Impairment of Fertility:

Studies with solutions from flexible plastic containers have not been performed to evaluate carcinogenic potential, mutagenic potential or effects on fertility.

PREGNANCY

Pregnancy Category C. Animal reproduction studies have not been conducted with dextrose, potassium chloride or sodium chloride. It is also not known whether dextrose, potassium chloride or sodium chloride can cause fetal harm when administered to a pregnant woman or can affect reproduction capacity. Dextrose, potassium chloride or sodium chloride should be given to a pregnant woman only if clearly needed.

Nursing Mothers:

Caution should be exercised when solutions from flexible plastic containers are administered to a nursing mother.

Pediatric Use:

The safety and effectiveness in the pediatric population are based on the similarity of the clinical conditions of the pediatric and adult populations. In neonates or very small infants the volume of fluid may affect fluid and electrolyte balance.

Frequent monitoring of serum glucose concentrations is required when dextrose is prescribed to pediatric patients, particularly neonates and low birth weight infants.

In very low birth weight infants, excessive or rapid administration of dextrose injection may result in increased serum osmolality and possible intracerebral hemorrhage.

Geriatric Use:

An evaluation of current literature revealed no clinical experience identifying differences in response between elderly and younger patients. In general, dose selection for an elderly patient should be cautious, usually starting at the low end of the dosing range, reflecting the greater frequency of decreased hepatic, renal, or cardiac function, and of concomitant disease or other drug therapy. Sodium and potassium ions are known to be substantially excreted by the kidney, and the risk of toxic reactions may be greater in patients with impaired renal function. Because elderly patients are more likely to have decreased renal function, care should be taken in dose selection, and it may be useful to monitor renal function.

ADVERSE REACTIONS

Reactions which may occur because of the solutions or technique of administration include febrile response, infection at the site of injection, venous thrombosis or phlebitis extending from the site of injection, extravasation and hypervolemia.

If an adverse reaction does occur, discontinue the infusion, evaluate the patient, institute appropriate therapeutic countermeasures and save the remainder of the fluid for examination if deemed necessary.

Nausea, vomiting, abdominal pain and diarrhea have been reported with potassium therapy. The signs and symptoms of potassium intoxication include paresthesias of the extremities, flaccid paralysis, listlessness, mental confusion, weakness and heaviness of the legs, hypotension, cardiac arrhythmias, heart block, electrocardiographic abnormalities such as disappearance of P waves, spreading and slurring of the QRS complex with development of a biphasic curve and cardiac arrest.

Potassium-containing solutions are intrinsically irritating to tissues. Therefore, extreme care should be taken to avoid perivascular infiltration. Local tissue necrosis and subsequent sloughing may result if extravasation occurs. Chemical phlebitis and venospasm have also been reported.

Should perivascular infiltration occur, I.V. administration at that site should be discontinued at once. Local infiltration of the affected area with procaine hydrochloride, 1%, to which hyaluronidase may be added, will often reduce venospasm and dilute the potassium remaining in the tissues locally. Local application of heat may also be helpful.

OVERDOSAGE

In the event of potassium overdosage, discontinue the infusion immediately and institute intensive corrective therapy to reduce serum potassium levels. See WARNINGS and PRECAUTIONS.

DOSAGE AND ADMINISTRATION

These solutions should be administered only by intravenous infusion and as directed by the physician. The dose and rate of injection are dependent upon the age, weight and clinical condition of the patient. If the serum potassium level is greater than 2.5 mEq/liter, potassium should be given at a rate not to exceed 10 mEq/hour in a concentration less than 30 mEq/liter. Somewhat faster rates and greater concentrations (usually up to 40 mEq/liter) of potassium may be indicated in patients with more severe potassium deficiency. The total 24-hour dose should not generally exceed 200 mEq of potassium.

As reported in the literature, the dosage and constant infusion rate of intravenous dextrose must be selected with caution in pediatric patients, particularly neonates and low birth weight infants, because of the increased risk of hyperglycemia/hypoglycemia.

Drug Interactions

Additives may be incompatible. Consult with pharmacist, if available. When introducing additives, use aseptic technique, mix thoroughly and do not store.

Parenteral drug products should be inspected visually for particulate matter and discoloration prior to administration, whenever solution and container permit. See PRECAUTIONS.

INSTRUCTIONS FOR USE

To Open

Tear outer wrap at notch and remove solution container. If supplemental medication is desired, follow directions below before preparing for administration. Some opacity of the plastic due to moisture absorption during the sterilization process may be observed. This is normal and does not affect the solution quality or safety. The opacity will diminish gradually.

To Add Medication

1. Prepare additive port.
2. Using aseptic technique and an additive delivery needle of appropriate length, puncture resealable additive port at target area, inner diaphragm and inject. Withdraw needle after injecting medication.
3. The additive port may be protected by covering with an additive cap.
4. Mix container contents thoroughly.

Preparation for Administration

(Use aseptic technique)

1. Close flow control clamp of administration set.
2. Remove cover from outlet port at bottom of container.
3. Insert piercing pin of administration set into port with a twisting motion until the set is firmly seated. NOTE: See full directions on administration set carton.
4. Suspend container from hanger.
5. Squeeze and release drip chamber to establish proper fluid level in chamber.
6. Open flow control clamp and clear air from set. Close clamp.
7. Attach set to venipuncture device. If device is not indwelling, prime and make venipuncture.
8. Regulate rate of administration with flow control clamp.

WARNING: Do not use flexible container in series connections.

HOW SUPPLIED

Intravenous solutions with potassium chloride (I.V. solution with KCl) are supplied in single-dose flexible plastic containers. See Tables:

TABLE 1
Potassium Chloride in 5% Dextrose and 0.225% Sodium Chloride Inj., USP |  | COMPOSITION (g/L) |  |  |  | Approx. Ionic Concentrations (mEq/L)
mEq Potassium | Size (mL) | Dextrose, Hydrous | Sodium Chloride | Potassium Chloride | Calculated Osmolarity (mOsmol/L) | pH | Sodium (Na+) | Potassium (K+) | Chloride (Cl–) | Approximate kcal/L | NDC NO.
20 mEq | 1000 | 50 | 2.25 | 1.49 | 370 | 4.2 (3.5 to 6.5) | 38.5 | 20 | 58.5 | 170 | 0409-7901-09^1
20 mEq | 1000 | 50 | 2.25 | 1.49 | 370 | 4.2 (3.5 to 6.5) | 38.5 | 20 | 58.5 | 170 | 0990-7901-09^1

ICU Medical is transitioning NDC codes from the "0409" to a "0990" labeler code. Both NDC codes are expected to be in the market for a period of time.

TABLE 2
Potassium Chloride in 5% Dextrose and 0.45% Sodium Chloride Inj., USP |  | COMPOSITION (g/L) |  |  |  | Approx. Ionic Concentrations (mEq/L)
mEq Potassium | Size (mL) | Dextrose, Hydrous | Sodium Chloride | Potassium Chloride | Calculated Osmolarity (mOsmol/L) | pH | Sodium (Na+) | Potassium (K+) | Chloride (Cl–) | Approximate kcal/L | NDC NO.
10 mEq | 1000 | 50 | 4.5 | 0.745 | 426 | 4.2 (3.5 to 6.5) | 77 | 10 | 87 | 170 | 0409-7993-09^2
10 mEq | 1000 | 50 | 4.5 | 0.745 | 426 | 4.2 (3.5 to 6.5) | 77 | 10 | 87 | 170 | 0990-7993-09^1,2
10 mEq | 500 | 50 | 4.5 | 1.49 | 447 | 4.2 (3.5 to 6.5) | 77 | 20 | 97 | 170 | 0409-7902-03^2
10 mEq | 500 | 50 | 4.5 | 1.49 | 447 | 4.2 (3.5 to 6.5) | 77 | 20 | 97 | 170 | 0990-7902-03^1,2
20 mEq | 1000 | 50 | 4.5 | 1.49 | 447 | 4.2 (3.5 to 6.5) | 77 | 20 | 97 | 170 | 0409-7902-09^1,2
20 mEq | 1000 | 50 | 4.5 | 1.49 | 447 | 4.2 (3.5 to 6.5) | 77 | 20 | 97 | 170 | 0990-7902-09^1,2
30 mEq | 1000 | 50 | 4.5 | 2.24 | 467 | 4.2 (3.5 to 6.5) | 77 | 30 | 107 | 170 | 0409-7903-09^1
30 mEq | 1000 | 50 | 4.5 | 2.24 | 467 | 4.2 (3.5 to 6.5) | 77 | 30 | 107 | 170 | 0990-7903-09^1
40 mEq | 1000 | 50 | 4.5 | 2.98 | 487 | 4.2 (3.5 to 6.5) | 77 | 40 | 117 | 170 | 0409-7904-09^1,2
40 mEq | 1000 | 50 | 4.5 | 2.98 | 487 | 4.2 (3.5 to 6.5) | 77 | 40 | 117 | 170 | 0990-7904-09^1,2

ICU Medical is transitioning NDC codes from the "0409" to a "0990" labeler code. Both NDC codes are expected to be in the market for a period of time.

TABLE 3
Potassium Chloride in 5% Dextrose and 0.9% Sodium Chloride Inj., USP |  | COMPOSITION (g/L) |  |  |  | Approx. Ionic Concentrations (mEq/L)
mEq Potassium | Size (mL) | Dextrose, Hydrous | Sodium Chloride | Potassium Chloride | Calculated Osmolarity (mOsmol/L) | pH | Sodium (Na+) | Potassium (K+) | Chloride (Cl–) | Approximate kcal/L | NDC NO.
20 mEq | 1000 | 50 | 9 | 1.49 | 600 | 4.2 (3.5 to 6.5) | 154 | 20 | 174 | 170 | 0409-7107-09^2
20 mEq | 1000 | 50 | 9 | 1.49 | 600 | 4.2 (3.5 to 6.5) | 154 | 20 | 174 | 170 | 0990-7107-09^1,2
40 mEq | 1000 | 50 | 9 | 2.98 | 640 | 4.2 (3.5 to 6.5) | 154 | 40 | 194 | 170 | 0409-7109-09^2
40 mEq | 1000 | 50 | 9 | 2.98 | 640 | 4.2 (3.5 to 6.5) | 154 | 40 | 194 | 170 | 0990-7109-09^1,2

ICU Medical is transitioning NDC codes from the "0409" to a "0990" labeler code. Both NDC codes are expected to be in the market for a period of time.

May contain HCl for pH adjustment.

Store at 20 to 25°C (68 to 77°F). [See USP Controlled Room Temperature.]

Protect from freezing.

Revised: December, 2020

^1Manufactured by ICU Medical, Inc., Lake Forest, Illinois, 60045, USA
^2Manufactured for ICU Medical, Inc., Lake Forest, Illinois, 60045, USA

IFU0000280

PRINCIPAL DISPLAY PANEL - 1000 mL Bag Label - IMP0000044

20 mEq POTASSIUM

1000 mL

NDC 0990-7107-09

20
mEq

POTASSIUM
CHLORIDE

in 5% Dextrose and
0.9% Sodium Chloride
Injection, USP

EACH 100 mL CONTAINS POTASSIUM
CHLORIDE 149 mg; SODIUM CHLORIDE
900 mg; DEXTROSE, HYDROUS 5 g IN WATER FOR
INJECTION. MAY CONTAIN HCl FOR pH
ADJUSTMENT. ELECTROLYTES PER 1000 mL
(NOT INCLUDING IONS FOR pH ADJUSTMENT):
POTASSIUM 20 mEq; SODIUM 154 mEq;
CHLORIDE 174 mEq.

600 mOsmol/LITER (CALC.)
pH 4.2 (3.5 to 6.5)

ADDITIVES MAY BE INCOMPATIBLE.
CONSULT WITH PHARMACIST, IF
AVAILABLE. WHEN INTRODUCING
ADDITIVES, USE ASEPTIC TECHNIQUE,
MIX THOROUGHLY AND DO NOT STORE.

SINGLE-DOSE CONTAINER. FOR I.V. USE.
USUAL DOSAGE: SEE INSERT. STERILE,
NONPYROGENIC. USE ONLY IF SOLUTION IS
CLEAR AND CONTAINER IS UNDAMAGED. MUST
NOT BE USED IN SERIES CONNECTIONS.

Rx only

3
v
CONTAINS DEHP

IMP0000044
ICU Medical, Inc.,
Lake Forest, Illinois, 60045, USA
icumedical

PRINCIPAL DISPLAY PANEL - 1000 mL Bag Label - IMP0000045

40 mEq POTASSIUM

1000 mL

NDC 0990-7109-09

40
mEq

POTASSIUM
CHLORIDE

in 5% Dextrose and
0.9% Sodium Chloride
Injection, USP

EACH 100 mL CONTAINS POTASSIUM CHLORIDE
298 mg; SODIUM CHLORIDE 900 mg; DEXTROSE,
HYDROUS 5 g IN WATER FOR INJECTION.
MAY CONTAIN HCl FOR pH ADJUSTMENT.
ELECTROLYTES PER 1000 mL (NOT INCLUDING
IONS FOR pH ADJUSTMENT): POTASSIUM
40 mEq; SODIUM 154 mEq; CHLORIDE 194 mEq.

640 mOsmol/LITER (CALC.)
pH 4.2 (3.5 to 6.5)

ADDITIVES MAY BE INCOMPATIBLE. CONSULT
WITH PHARMACIST, IF
AVAILABLE. WHEN INTRODUCING
ADDITIVES, USE ASEPTIC TECHNIQUE,
MIX THOROUGHLY AND DO NOT STORE.

SINGLE-DOSE CONTAINER. FOR I.V. USE.
USUAL DOSAGE: SEE INSERT. STERILE,
NONPYROGENIC. USE ONLY IF SOLUTION IS
CLEAR AND CONTAINER IS UNDAMAGED.
MUST NOT BE USED IN SERIES CONNECTIONS.

Rx ONLY

3
v
CONTAINS DEHP

IMP0000045
ICU Medical, Inc.,
Lake Forest, Illinois, 60045, USA
icumedical

PRINCIPAL DISPLAY PANEL - 1000 mL Bag Label - IM-4420

30 mEq POTASSIUM

1000 mL

NDC 0990-7903-09

30
mEq

POTASSIUM
CHLORIDE

in 5% Dextrose and
0.45% Sodium Chloride
Injection, USP

EACH 100 mL CONTAINS POTASSIUM CHLORIDE
224 mg; SODIUM CHLORIDE 450 mg; DEXTROSE,
HYDROUS 5 g IN WATER FOR INJECTION.
MAY CONTAIN HCl FOR pH ADJUSTMENT.
ELECTROLYTES PER 1000 mL (NOT INCLUDING
IONS FOR pH ADJUSTMENT): POTASSIUM
30 mEq; SODIUM 77 mEq; CHLORIDE 107 mEq.

467 mOsmol/LITER (CALC.)
pH 4.2 (3.5 to 6.5)

ADDITIVES MAY BE INCOMPATIBLE.
CONSULT WITH PHARMACIST, IF
AVAILABLE. WHEN INTRODUCING
ADDITIVES, USE ASEPTIC TECHNIQUE,
MIX THOROUGHLY AND DO NOT STORE.

SINGLE-DOSE CONTAINER. FOR I.V. USE.
USUAL DOSAGE: SEE INSERT. STERILE,
NONPYROGENIC. USE ONLY IF SOLUTION IS
CLEAR AND CONTAINER IS UNDAMAGED.
MUST NOT BE USED IN SERIES CONNECTIONS.

Rx ONLY

3
v
CONTAINS DEHP

IM-4420
ICU Medical, Inc., Lake Forest, Illinois, 60045, USA
icumedical

PRINCIPAL DISPLAY PANEL - 1000 mL Bag Label - IM-4421

40 mEq POTASSIUM

1000 mL

NDC 0990-7904-09

40
mEq

POTASSIUM
CHLORIDE

in 5% Dextrose and
0.45% Sodium Chloride
Injection, USP

EACH 100 mL CONTAINS POTASSIUM CHLORIDE
298 mg; SODIUM CHLORIDE 450 mg; DEXTROSE,
HYDROUS 5 g IN WATER FOR INJECTION.
MAY CONTAIN HCl FOR pH ADJUSTMENT.
ELECTROLYTES PER 1000 mL (NOT INCLUDING
IONS FOR pH ADJUSTMENT): POTASSIUM
40 mEq; SODIUM 77 mEq; CHLORIDE 117 mEq.

487 mOsmol/LITER (CALC.)
pH 4.2 (3.5 to 6.5)

ADDITIVES MAY BE INCOMPATIBLE.
CONSULT WITH PHARMACIST, IF
AVAILABLE. WHEN INTRODUCING
ADDITIVES, USE ASEPTIC TECHNIQUE,
MIX THOROUGHLY AND DO NOT STORE.

SINGLE-DOSE CONTAINER. FOR I.V. USE.
USUAL DOSAGE: SEE INSERT. STERILE,
NONPYROGENIC. USE ONLY IF SOLUTION IS
CLEAR AND CONTAINER IS UNDAMAGED.
MUST NOT BE USED IN SERIES CONNECTIONS.

Rx ONLY

3
v
CONTAINS DEHP

IM-4421
ICU Medical, Inc., Lake Forest, Illinois, 60045, USA
icumedical

PRINCIPAL DISPLAY PANEL - 1000 mL Bag Label - IMP0000057

10 mEq POTASSIUM

1000 mL

NDC 0990-7993-09

10
mEq

POTASSIUM
CHLORIDE

in 5% Dextrose and
0.45% Sodium Chloride
Injection, USP

EACH 100 mL CONTAINS POTASSIUM
CHLORIDE 74.5 mg; SODIUM CHLORIDE 450 mg;
DEXTROSE, HYDROUS 5 g IN WATER FOR
INJECTION. MAY CONTAIN HCl FOR pH
ADJUSTMENT.

ELECTROLYTES PER 1000 mL (NOT INCLUDING
IONS FOR pH ADJUSTMENT): POTASSIUM
10 mEq; SODIUM 77 mEq; CHLORIDE 87 mEq.

426 mOsmol/LITER (CALC.)
pH 4.2 (3.5 to 6.5)

ADDITIVES MAY BE INCOMPATIBLE.
CONSULT WITH PHARMACIST, IF AVAILABLE.
WHEN INTRODUCING ADDITIVES,
USE ASEPTIC TECHNIQUE, MIX THOROUGHLY
AND DO NOT STORE.

SINGLE-DOSE CONTAINER. FOR I.V. USE.
USUAL DOSAGE: SEE INSERT. STERILE,
NONPYROGENIC. USE ONLY IF SOLUTION IS
CLEAR AND CONTAINER IS UNDAMAGED.
MUST NOT BE USED IN SERIES CONNECTIONS.

Rx ONLY

3
v
CONTAINS
DEHP

IMP0000057
ICU Medical, Inc.
Lake Forest, Illinois, 60045 USA
icumedical

PRINCIPAL DISPLAY PANEL - 1000 mL Bag Label - IM-4418

20 mEq POTASSIUM

1000 mL

NDC 0990-7901-09

20
mEq

POTASSIUM
CHLORIDE
in 5% Dextrose and
0.225% Sodium Chloride
Injection, USP

EACH 100 mL CONTAINS POTASSIUM CHLORIDE
149 mg; SODIUM CHLORIDE 225 mg; DEXTROSE,
HYDROUS 5 g IN WATER FOR INJECTION.
MAY CONTAIN HCl FOR pH ADJUSTMENT.
ELECTROLYTES PER 1000 mL (NOT INCLUDING
IONS FOR pH ADJUSTMENT): POTASSIUM
20 mEq; SODIUM 38.5 mEq; CHLORIDE 58.5 mEq.

370 mOsmol/LITER (CALC.)
pH 4.2 (3.5 to 6.5)

ADDITIVES MAY BE INCOMPATIBLE.
CONSULT WITH PHARMACIST, IF
AVAILABLE. WHEN INTRODUCING
ADDITIVES, USE ASEPTIC TECHNIQUE,
MIX THOROUGHLY AND DO NOT STORE.

SINGLE-DOSE CONTAINER. FOR I.V. USE.
USUAL DOSAGE: SEE INSERT. STERILE,
NONPYROGENIC. USE ONLY IF SOLUTION IS
CLEAR AND CONTAINER IS UNDAMAGED.
MUST NOT BE USED IN SERIES CONNECTIONS.

©HOSPIRA 2004
IM-0057 (4/04)
PRINTED IN USA
HOSPIRA, INC., LAKE FOREST, IL 60045 USA

Rx ONLY

3
v
CONTAINS DEHP

IM-4418
ICU Medical, Inc., Lake Forest, Illinois, 60045, USA
icumedical

PRINCIPAL DISPLAY PANEL - 500 mL Bag Label - IM-4447

10 mEq POTASSIUM

500 mL

NDC 0990-7902-03

10
mEq

POTASSIUM
CHLORIDE
in 5% Dextrose and
0.45% Sodium Chloride Inj., USP

EACH 100 mL CONTAINS POTASSIUM CHLORIDE 149 mg;
SODIUM CHLORIDE 450 mg; DEXTROSE, HYDROUS 5 g IN WATER
FOR INJECTION. MAY CONTAIN HCl FOR pH ADJUSTMENT.
ELECTROLYTES PER 1000 mL (NOT INCLUDING IONS FOR pH
ADJUSTMENT): POTASSIUM 20 mEq; SODIUM 77 mEq; CHLORIDE 97 mEq.

447 mOsmol/LITER (CALC.)
pH 4.2 (3.5 to 6.5)

ADDITIVES MAY BE INCOMPATIBLE. CONSULT WITH
PHARMACIST, IF AVAILABLE. WHEN INTRODUCING
ADDITIVES, USE ASEPTIC TECHNIQUE, MIX
THOROUGHLY AND DO NOT STORE.

SINGLE-DOSE CONTAINER. FOR I.V. USE. USUAL DOSAGE: SEE INSERT.
STERILE, NONPYROGENIC. USE ONLY IF SOLUTION IS CLEAR AND CONTAINER
IS UNDAMAGED. MUST NOT BE USED IN SERIES CONNECTIONS.

Rx ONLY

3
v
CONTAINS DEHP

ICU Medical, Inc., Lake Forest, Illinois, 60045, USA
IM-4447
icumedical

PRINCIPAL DISPLAY PANEL - Overwrap

TO OPEN TEAR AT NOTCH

2
HDPE

DO NOT REMOVE FROM OVERWRAP UNTIL READY FOR USE. AFTER REMOVING
THE OVERWRAP, CHECK FOR MINUTE LEAKS BY SQUEEZING CONTAINER FIRMLY.
IF LEAKS ARE FOUND, DISCARD SOLUTION AS STERILITY MAY BE IMPAIRED.
RECOMMENDED STORAGE: ROOM TEMPERATURE (25°C). AVOID EXCESSIVE
HEAT. PROTECT FROM FREEZING. SEE INSERT.
98-4321-R14-3/98